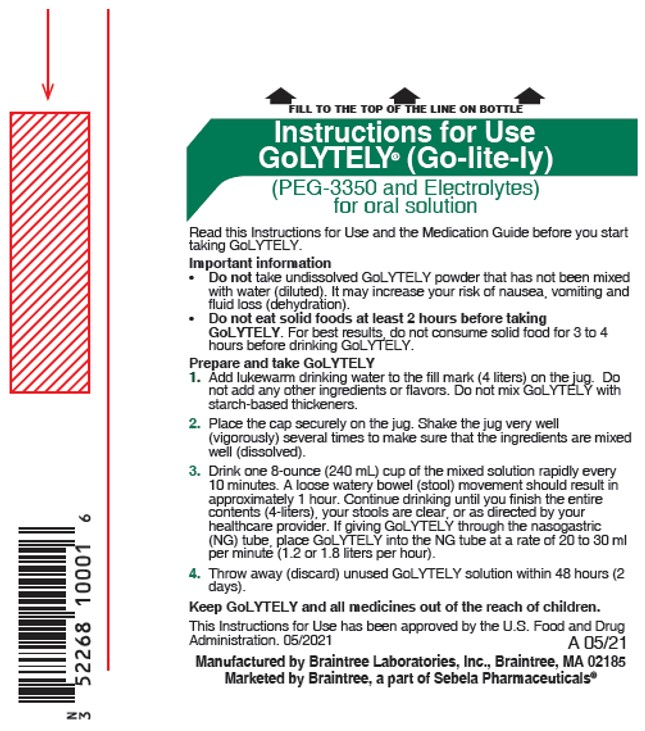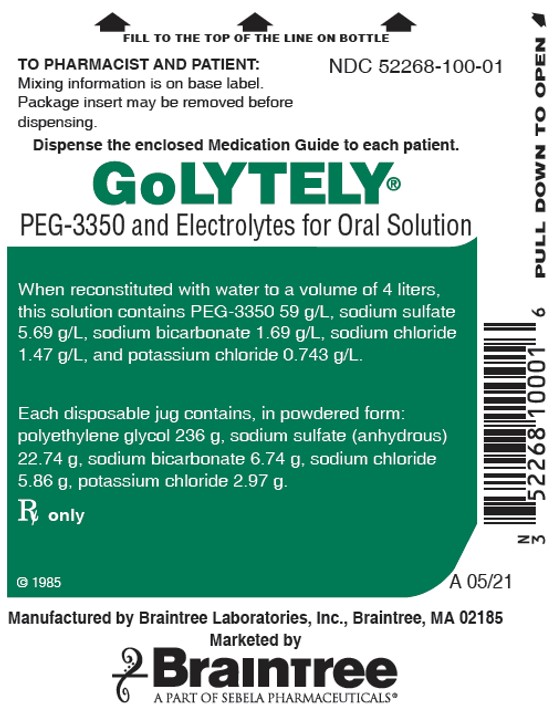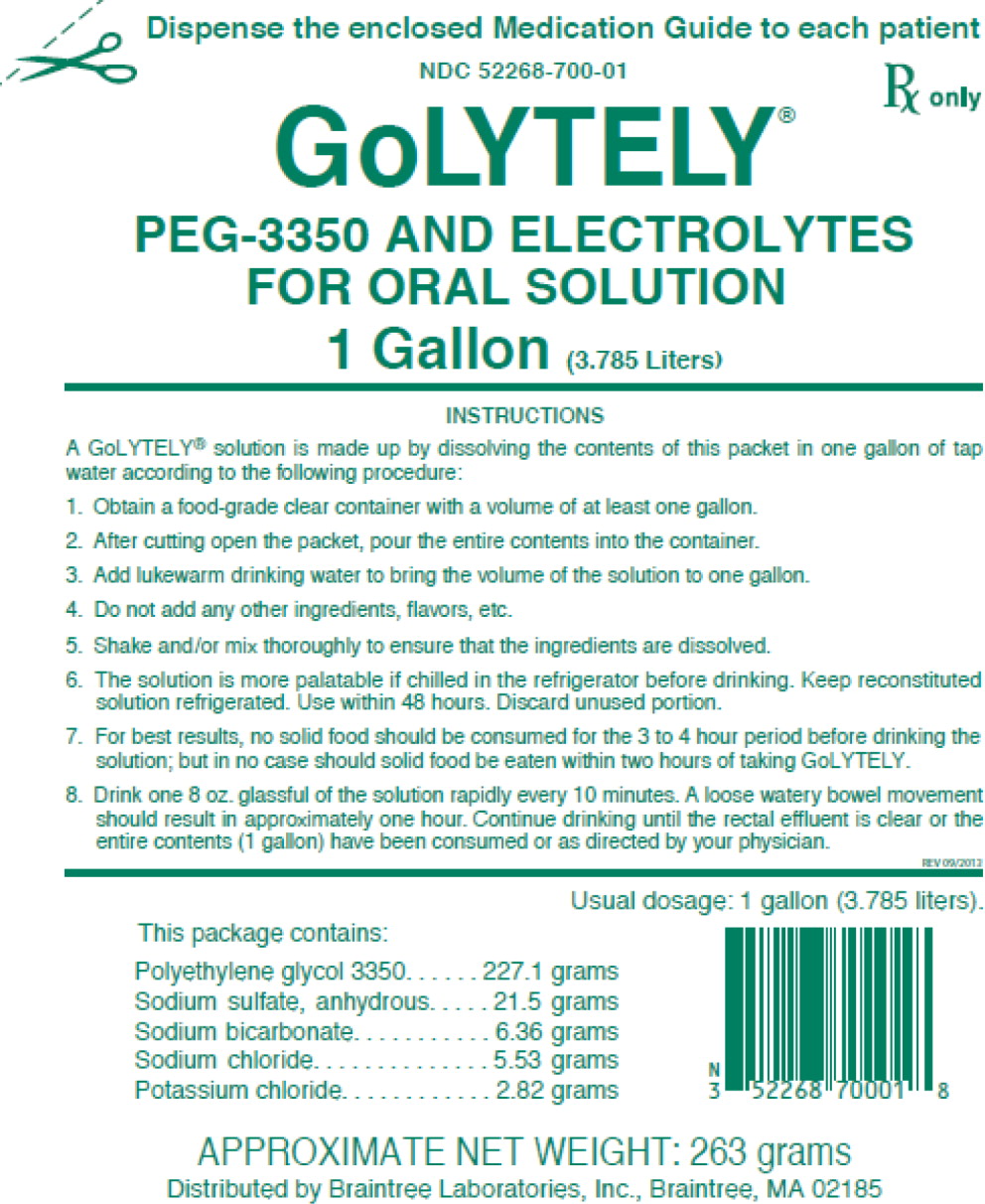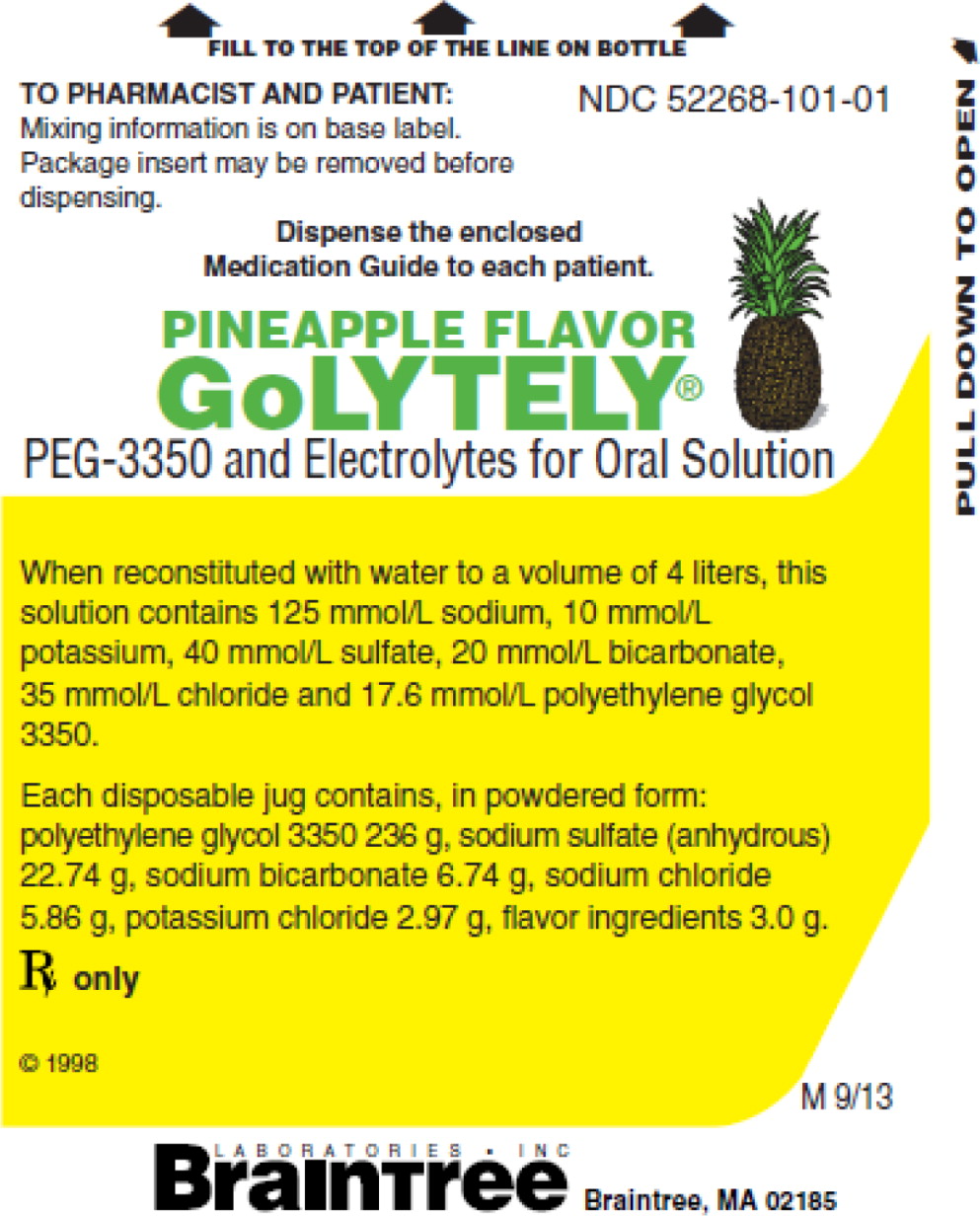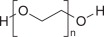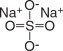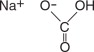 DRUG LABEL: GoLYTELY
NDC: 52268-100 | Form: POWDER, FOR SOLUTION
Manufacturer: Braintree Laboratories, Inc.
Category: prescription | Type: HUMAN PRESCRIPTION DRUG LABEL
Date: 20210528

ACTIVE INGREDIENTS: POLYETHYLENE GLYCOL 3350 236 g/4 L; SODIUM SULFATE ANHYDROUS 22.74 g/4 L; SODIUM BICARBONATE 6.74 g/4 L; SODIUM CHLORIDE 5.86 g/4 L; POTASSIUM CHLORIDE 2.97 g/4 L

HIGHLIGHTS OF PRESCRIBING INFORMATION

These highlights do not include all the information needed to use GOLYTELY safely and effectively. See full prescribing information for GOLYTELY.
GOLYTELY (polyethylene glycol 3350 and electrolytes for oral solution)
Initial U.S. Approval: 1984

RECENT MAJOR CHANGES

Warnings and Precautions, Aspiration: (5.7) | 05/2021

1 INDICATIONS AND USAGE

GoLYTELY is a combination of PEG 3350, an osmotic laxative, and electrolytes indicated for cleansing of the colon in preparation for colonoscopy and barium enema X-ray examination in adults (1)

2 DOSAGE AND ADMINISTRATION

Preparation and Administration (2.1):

- Correct fluid and electrolyte abnormalities before treatment with GoLYTELY.
- Reconstitute GoLYTELY with water prior to ingestion.
- Do not take oral medications within 1 hour before the start or during administration of GoLYTELY. (2.1)
- Do not take other laxatives while taking GoLYTELY.
- Consume only clear liquids; avoid red and purple liquids.
- Consume water or other clear liquids up until 2 hours before the time of the colonoscopy.
- Do not consume solid food within 2 hours before starting GoLYTELY.

Adult Dosing Regimen (2.2):

- On day prior to colonoscopy, instruct patients to consume a light breakfast at least 2 hours before starting GoLYTELY.
- Begin the recommended dosage regimen for GoLYTELY early in the evening on the day before colonoscopy
- Drink reconstituted solution at a rate of 8 ounces every 10 minutes, until 4 liters are consumed, or rectal effluent is clear.
- For complete information on dosing, preparation and administration, see the full prescribing information. (2.1, 2.2)

3 DOSAGE FORMS AND STRENGTHS

For Oral Solution: 236 g polyethylene glycol 3350, 22.74 g sodium sulfate (anhydrous), 6.74 g sodium bicarbonate, 5.86 g sodium chloride and 2.97 g potassium chloride per 4 liters.

4 CONTRAINDICATIONS

- Gastrointestinal (GI) obstruction (4, 5.6)
- Bowel perforation (4, 5.6)
- Toxic colitis or toxic megacolon (4)
- Gastric retention (4)
- Ileus (4)
- Hypersensitivity to components of GoLYTELY (4, 5.8)

5 WARNINGS AND PRECAUTIONS

- Risk of fluid and electrolyte abnormalities: Encourage adequate hydration, assess concurrent medications, and consider laboratory assessments prior to and after use. (5.1, 5.2, 7.1)
- Cardiac arrhythmias: Consider pre-dose and post-colonoscopy ECGs in patients at increased risk of serious cardiac arrhythmias. (5.2)
- Seizures: Use caution in patients with a history of seizures and patients at increased risk of seizure, including medications that lower the seizure threshold. (5.3, 7.1)
- Patients with renal impairment or taking concomitant medications that affect renal function: Use caution, ensure adequate hydration and consider testing. (5.4, 7.1, 8.6)
- Mucosal ulcerations: Consider potential for mucosal ulcerations when interpreting colonoscopy findings in patients with known or suspected
  inflammatory bowel disease. (5.5, 7.3)
- Patients at risk for aspiration: Observe during administration. (5.7)
- Hypersensitivity reactions including anaphylaxis: Inform patients to seek immediate medical care if symptoms occur. (5.8)

6 ADVERSE REACTIONS

Most common adverse reactions are: nausea, abdominal fullness, bloating, abdominal cramps, vomiting and anal irritation. (6)

To report SUSPECTED ADVERSE REACTIONS, contact Braintree Laboratories, Inc. at 1-800-874-6756 or FDA at 1-800-FDA-1088 or www.fda.gov/medwatch.

7 DRUG INTERACTIONS

Some drugs increase risks due to fluid and electrolyte changes (7.1)

FULL PRESCRIBING INFORMATION

1 INDICATIONS AND USAGE

GoLYTELY is indicated for bowel cleansing prior to colonoscopy and barium enema X-ray examination in adults.

2 DOSAGE AND ADMINISTRATION

2.1 Important Preparation and Administration Instructions

- Correct fluid and electrolyte abnormalities before treatment with GoLYTELY [see Warnings and Precautions (5.1)] .
- Reconstitute GoLYTELY with water prior to ingestion, do not take undissolved GoLYTELY [see Dosage and Administration (2.2)] . Do not reconstitute with other liquids and/or add starch-based thickeners to the mixing container [see Warnings and Precautions (5.7)] .
- Do not take oral medications within 1 hour before the start of or during administration of GoLYTELY [see Drug Interactions (7.2)] .
- Do not take other laxatives while taking GoLYTELY [see Drug Interactions (7.3)] .
- Consume only clear liquids, avoid red and purple liquids.
- Patients may consume water or other clear liquids during the bowel preparation and after completion of the bowel preparation up until 2 hours before the time of the colonoscopy.
- The solution is more palatable if chilled prior to administration.
- Do not consume solid food within 2 hours before starting GoLYTELY. For the best results, do not consume solid food for 3 to 4 hours before drinking the solution.
- If severe bloating, distention or abdominal pain occurs, slow or temporarily discontinue GoLYTELY until the symptoms abate.

2.2 Dosage Regimen

Instruct adult patients that on the day before the colonoscopy procedure, they may consume a light breakfast at least 2 hours before starting GoLYTELY. Begin the recommended dosage regiment for GoLYTELY early in the evening on the day before colonoscopy.

Instruct patients to take GoLYTELY in conjunction with clear liquids as follows:

4 Liter Jug

- Fill the supplied container containing the GoLYTELY powder with lukewarm drinking water to the 4-liter fill line
- Do not add any other ingredients, flavors, etc.
- After capping the container, shake vigorously several times to ensure that the ingredients are dissolved.
- Drink at a rate of 8 ounces every 10 minutes until the entire contents are consumed or the rectal effluent is clear. A loose watery bowel movement should result in approximately one hour.
- After reconstitution, keep solution refrigerated 2° to 8°C (36° to 46°F). Do not freeze. Use within 48 hours, discard unused portion.

Administration via a Nasogastric Tube

For patients with a nasogastric tube, administer the reconstituted GoLYTELY solution at a rate of 20 to 30 mL per minute (1.2 to 1.8 liters per hour).

3 DOSAGE FORMS AND STRENGTHS

For Oral Solution: 236 g polyethylene glycol 3350, 22.74 g sodium sulfate (anhydrous), 6.74 g sodium bicarbonate, 5.86 g sodium chloride and 2.97 g potassium chloride as a white powder. When reconstituted with water to a volume of 4 liters, the solution contains 59 g/L PEG-3350, 5.69 g/L sodium sulfate, 1.69 g/L sodium bicarbonate, 1.47 g/L sodium chloride and 0.743 g/L potassium chloride.

4 CONTRAINDICATIONS

GoLYTELY is contraindicated in the following conditions:

- Gastrointestinal (GI) obstruction [see Warnings and Precautions (5.6)]
- Bowel perforation [see Warnings and Precautions (5.6)]
- Toxic colitis or toxic megacolon
- Gastric retention
- Ileus
- Hypersensitivity to any component of GoLYTELY [see Warnings and Precautions (5.8)]

5 WARNINGS AND PRECAUTIONS

5.1 Serious Fluid and Serum Chemistry Abnormalities

Advise patients to hydrate adequately before, during, and after the use of GoLYTELY. Use caution in patients with congestive heart failure when replacing fluids. If a patient develops significant vomiting or signs of dehydration including signs of orthostatic hypotension after taking GoLYTELY, consider performing post-colonoscopy lab tests (electrolytes, creatinine, and BUN) and treat accordingly. Fluid and electrolyte disturbances can lead to serious adverse events including cardiac arrhythmias, seizures and renal impairment. Correct fluid and electrolyte abnormalities before treatment with GoLYTELY.

In addition, use caution when prescribing GoLYTELY for patients who have conditions, or who are using medications, that increase the risk for fluid and electrolyte disturbances or may increase the risk of adverse events of seizure, arrhythmias, and renal impairment [ see Drug Interactions (7.1) ].

5.2 Cardiac Arrythmias

There have been rare reports of serious arrhythmias associated with the use of ionic osmotic laxative products for bowel preparation. Use caution when prescribing GoLYTELY for patients at increased risk of arrhythmias (e.g., patients with a history of prolonged QT, uncontrolled arrhythmias, recent myocardial infarction, unstable angina, congestive heart failure, or cardiomyopathy). Consider pre-dose and post-colonoscopy ECGs in patients at increased risk of serious cardiac arrhythmias.

5.3 Seizures

There have been reports of generalized tonic-clonic seizures and/or loss of consciousness associated with use of bowel preparation products in patients with no prior history of seizures. The seizure cases were associated with electrolyte abnormalities (e.g., hyponatremia, hypokalemia, hypocalcemia, and hypomagnesemia) and low serum osmolality. The neurologic abnormalities resolved with correction of fluid and electrolyte abnormalities.

Use caution when prescribing GoLYTELY for patients with a history of seizures and in patients at increased risk of seizure, such as patients taking medications that lower the seizure threshold (e.g., tricyclic antidepressants), patients withdrawing from alcohol or benzodiazepines, or patients with known or suspected hyponatremia [see Drug Interactions (7.1)] .

5.4 Renal Impairment

Use caution when prescribing GoLYTELY for patients with impaired renal function or patients taking concomitant medications that may affect renal function (such as diuretics, angiotensin converting enzyme inhibitors, angiotensin receptor blockers, or non-steroidal anti-inflammatory drugs) [see Drug Interactions (7.1)] . Advise these patients of the importance of adequate hydration and consider performing baseline and post-colonoscopy laboratory tests (electrolytes, creatinine, and BUN) in these patients [see Use is Specific Populations (8.6)] .

5.5 Colonic Mucosal Ulcerations and Ischemic Colitis

Administration of osmotic laxative products may produce colonic mucosal aphthous ulcerations, and there have been reports of more serious cases of ischemic colitis requiring hospitalization. Concurrent use of stimulant laxatives and GoLYTELY may increase this risk [see Drug Interactions (7.3)] . Consider the potential for mucosal ulcerations resulting from the bowel preparation when interpreting colonoscopy findings in patients with known or suspect inflammatory bowel disease (IBD).

5.6 Use in Patients with Significant Gastrointestinal Disease

If gastrointestinal obstruction or perforation is suspected, perform appropriate diagnostic studies to rule out these conditions before administering GoLYTELY [see Contraindications (4)] . Use with caution in patients with severe active ulcerative colitis.

5.7 Aspiration

Use with caution in patients with impaired gag reflex, unconscious, or semiconscious patients, and patients prone to regurgitation or aspiration. Observe these patients during administration of GoLYTELY, especially if it is administered via nasogastric tube.Use with caution in patients with impaired gag reflex, unconscious, or semiconscious patients, and patients prone to regurgitation or aspiration. Observe these patients during administration of GoLYTELY, especially if it is administered via nasogastric tube.

Do not combine GoLYTELY with starch-based thickeners [see Dosage and Administration (2.1)] . Polyethylene glycol (PEG), a component of GoLYTELY, when mixed with starch- thickened liquids reduces the viscosity of the starch-thickened liquid. When a PEG-based product used for another indication was mixed in starch-based pre-thickened liquids used in patients with dysphagia, thinning of the liquid occurred and cases of choking and potential aspiration were reported.

5.8 Hypersensitivity Reactions

GoLYTELY contains PEG and may cause serious hypersensitivity reactions including anaphylaxis, angioedema, rash, urticaria, and pruritus [see Adverse Reactions (6)] . Inform patients of the signs and symptoms of anaphylaxis and instruct them to seek immediate medical care should signs and symptoms occur.

6 ADVERSE REACTIONS

The following clinically significant adverse reactions are described elsewhere in the labeling:

- Renal impairment [see Warnings and Precautions (5.4)]
- Colonic mucosal ulcerations and ischemic colitis [see Warnings and Precautions (5.5)]
- Patients with significant gastrointestinal disease [see Warnings and Precautions (5.6)]
- Aspiration [see Warnings and Precautions (5.7)]

The following adverse reactions associated with the use of GoLYTELY were identified in clinical trials or postmarketing reports. Because these reactions are reported voluntarily from a population of uncertain size, it is not always possible to estimate their frequency, reliably, or establish a causal relationship to drug exposure.

- Cardiovascular: arrhythmia, atrial fibrillation, peripheral edema, asystole, and acute pulmonary edema after aspiration [see Warnings and Precautions (5.2)] .

- Nervous system: tremor, seizure [see Warnings and Precautions (5.3)]

- Hypersensitivity: Urticaria/rash, pruritus, dermatitis, rhinorrhea, dyspnea, chest and throat tightness, fever, angioedema, anaphylaxis and anaphylactic shock [see Contraindications (4), Warnings and Precautions (5.8)]

- Gastrointestinal: Nausea, abdominal fullness and bloating are the most common adverse reactions (occurred in up to 50% of patients). Other less common adverse reactions include: abdominal cramps, vomiting, “butterfly-like” infiltrates on chest X-ray after vomiting and aspirating PEG, anal irritation, and upper GI bleeding from Mallory-Weiss Tear, esophageal perforation [usually with gastroesophageal reflux disease (GERD)].

7 DRUG INTERACTIONS

7.1 Drugs that May Increase Risks Due to Fluid and Electrolyte Abnormalities

Use caution when prescribing GoLYTELY for patients with conditions and/or who are using medications that increase the risk for fluid and electrolyte disturbances or may increase the risk of renal impairment, seizure, arrhythmias, and prolonged QT in the setting of fluid and electrolyte abnormalities [ see Warnings and Precautions (5.1, 5.2, 5.3, 5.4) ]. Consider additional patient evaluations as appropriate.

7.2 Potential for Reduced Drug Absorption

GoLYTELY can reduce the absorption of other administered drugs. Administer oral medications within one hour before the start of administration of GoLYTELY [see Dosage and Administration (2.1)] .

7.3 Stimulant Laxatives

Concurrent use of stimulant laxatives and GoLYTELY may increase the risk of mucosal ulceration or ischemic colitis. Avoid use of stimulant laxatives (e.g., bisacodyl, sodium picosulfate) while taking GoLYTELY [see Warnings and Precautions (5.5)] .

8 USE IN SPECIFIC POPULATIONS

8.1 Pregnancy

Animal reproduction studies have not been conducted with GoLYTELY. It is also not known whether GoLYTELY can cause fetal harm when administered to a pregnant woman or can affect reproductive capacity. GoLYTELY should be given to a pregnant woman only if clearly needed.

8.3 Nursing Mothers

It is not known whether this drug is excreted in human milk. Because many drugs are excreted in human milk, caution should be exercised when GoLYTELY is administered to a nursing woman.

8.4 Pediatric Use

Safety and effectiveness of GoLYTELY in pediatric patients have not been established.

8.5 Geriatric Use

Clinical studies of GoLYTELY did not include sufficient numbers of subjects aged 65 and over to determine whether they respond differently from younger subjects. Other reported clinical experience has not identified differences in responses between the elderly and younger patients.

8.6 Renal Impairment

Use GoLYTELY with caution in patients with renal impairment or patients taking concomitant medications that may affect renal function [see Drug Interactions (7.1)] . These patients may be at risk for renal injury. Advise these patients of the importance of adequate hydration before, during and after use of GoLYTELY and consider performing baseline and post-colonoscopy laboratory tests (electrolytes, creatinine, and BUN) in these patients [see Warnings and Precautions (5.4)] .

11 DESCRIPTION

GoLYTELY is a combination of polyethylene glycol 3350, an osmotic laxative, and electrolytes (sodium sulfate, sodium chloride, sodium bicarbonate and potassium chloride) for oral solution supplied in a 4-liter disposable jug containing 236 g polyethylene glycol 3350, 22.74 g sodium sulfate (anhydrous), 6.74 g sodium bicarbonate, 5.86 g sodium chloride, and 2.97 g potassium chloride as a white powder.

Polyethylene Glycol 3350, USP

Sodium Sulfate, USP

The chemical name is Na2SO4. The average Molecular Weight is 142.04. The structural formula is:

Sodium Bicarbonate, USP

The chemical name is NaHCO3. The average Molecular Weight is 84.01. The structural formula is:

Sodium Chloride, USP

The chemical name is NaCl. The average Molecular Weight: 58.44. The structural formula is:

Na^+ Cl^-

Potassium Chloride, USP

The chemical name is KCl. The average Molecular Weight: 74.55. The structural formula is:

K-Cl

12 CLINICAL PHARMACOLOGY

12.1 Mechanism of Action

The primary mode of action is thought to be through the osmotic effect of polyethylene glycol 3350 which causes water to be retained in the colon and produces a watery stool.

12.2 Pharmacodynamics

GoLYTELY induces as diarrhea which rapidly cleanses the bowel, usually within four hours.

12.3 Pharmacokinetics

The pharmacokinetics of PEG3350 following administration of GoLYTELY were not assessed. Available pharmacokinetic information for oral PEG3350 suggests that it is poorly absorbed.

16 HOW SUPPLIED/STORAGE AND HANDLING

GoLYTELY (polyethylene glycol 3350 and electrolytes for oral solution) is supplied in a 4-liter disposable jug containing 236 g polyethylene glycol 3350, 22.74 g sodium sulfate (anhydrous), 6.74 g sodium bicarbonate, 5.86 g sodium chloride and 2.97 g potassium chloride as a white powder.

- When reconstituted with water to a volume of 4 liters, the solution contains 59 g/L PEG-3350, 5.69 g/L sodium sulfate, 1.69 g/L sodium bicarbonate, 1.47 g/L sodium chloride and 0.743 g/L potassium chloride.

GoLYTELY 4 Liter Disposable Jug NDC 52268-100-01

Storage

Store in sealed container at 15° to 30°C (59° to 86°F).

Store reconstituted solution of GoLYTELY at 2° to 8°C (36° to 46°F). Do not freeze [see Dosage and Administration (2.1)] .

17 PATIENT COUNSELING INFORMATION

Advise the patient to read the FDA-Approved Patient Labeling (Medication Guide and Instructions for Use).

Instruct Patients:

- To reconstitute GoLYTELY with water prior to ingestion.
- Not to take other laxatives while they are taking GoLYTELY.
- Not to take oral medications within 1 hour before the start or during the administration of GoLYTELY.
- To take only clear liquids but avoid red and purple liquids.
- To consume water or other clear liquids during the bowel preparation and after completion of the bowel preparation up until 2 hours before the time of the colonoscopy.
- To follow the directions in the Instructions for Use on how to prepare and administer the product.
- If they experience severe bloating, distention or abdominal pain, to slow or temporarily discontinue drinking the solution and to contact their healthcare provider.
- To contact their healthcare provider if they develop signs and symptoms of dehydration or if they experience altered consciousness or seizures. [see Warnings and Precautions (5.1, 5.2, 5.3, 5.4)] .
- To discontinue administration of the solution and contact their healthcare provider if they develop symptoms of a hypersensitivity reaction [see Warnings and Precautions (5.8)] .

Manufactured by Braintree Laboratories, Inc. 270 Centre Street Holbrook, MA 02343

Marketed by Braintree, a Part of Sebela Pharmaceuticals®. 60 Columbian Street West Braintree, MA 02185

Medication Guide

GoLYTELY® (Go-lite-ly)

(PEG-3350 and Electrolytes)

for oral solution

Read this Medication Guide before you start taking GoLYTELY. This information does not take the place of talking with your healthcare provider about your medical condition or your treatment.

What is the most important information I should know about GoLYTELY?

GoLYTELY and other osmotic bowel preparations can cause serious side effects, including:

Serious loss of body fluid (dehydration) and changes in blood salts (electrolytes) in your blood.
These changes can cause:

- abnormal heartbeats (arrhythmias) that can cause death.
- seizures. This can happen even if you have never had a seizure.
- kidney problems.

Your chance of having fluid loss and changes in body salts with GoLYTELY is higher if you:

- have heart problems.
- have kidney problems.
- take water pills or non-steroidal anti-inflammatory drugs (NSAIDS).

Tell your healthcare provider right away if you have any of these symptoms of a loss of too much body fluid
(dehydration) while taking GoLYTELY:

- vomiting that prevents you from keeping down the solution.
- dizziness.
- urinating less often than normal.
- headache.

See Section “What are the possible side effects of GoLYTELY” for more information about side effects.

What is GoLYTELY?

GoLYTELY is a prescription medicine used by adults to clean the colon before a colonoscopy or barium enema X-ray examination. GoLYTELY cleans your colon by causing you to have diarrhea (loose stools). Cleaning your colon helps your healthcare provider see the inside of your colon more clearly during your colonoscopy. It is not known if GoLYTELY is safe and effective in children.

Who should not take GoLYTELY?

Do not take GoLYTELY if your healthcare provider has told you that you have:

- a blockage in your bowel (obstruction).
- an opening in the wall of your stomach or intestine (bowel perforation).
- a very dilated intestine (toxic megacolon).
- problems with food and fluid emptying from your stomach (gastric retention).
- a problem with food moving too slowly through your intestines (ileus).
- an allergy to any of the ingredients in GoLYTELY. See the end of this Medication Guide for a complete list of ingredients in GoLYTELY.

What should I tell my healthcare provider before taking GoLYTELY?
Before you take GoLYTELY, tell your healthcare provider if you:

- have heart problems.
- have stomach or bowel problems.
- have ulcerative colitis.
- have problems with swallowing or gastric reflux.
- have a history of seizures.
- are withdrawing from drinking alcohol.
- have a low blood salt (sodium) level.
- have kidney problems.
- have any other medical conditions.
- are pregnant. It is not known if GoLYTELY will harm your unborn baby. Talk to your doctor if you are pregnant or plan to become pregnant.
- are breastfeeding or plan to breastfeed. It is not known if GoLYTELY passes into your breast milk. You and your healthcare provider should decide if you will take GoLYTELY while breastfeeding.

Tell your healthcare provider about all the medicines you take, including prescription and over-the-counter medicines, vitamins, and herbal supplements.

GoLYTELY may affect how other medicines work. Do not take medicines by mouth within 1 hour of starting GoLYTELY or after you start taking GoLYTELY. Especially tell your healthcare provider if you take:

- medicines for blood pressure or heart problems.
- medicines for kidney problems.
- medicines for seizures.
- water pills (diuretics).
- non-steroidal anti-inflammatory medicines (NSAID) pain medicines.
- laxatives.
- starch-based thickeners. For patients who have trouble swallowing, do not mix GoLYTELY with starch-based thickeners.

Ask your healthcare provider or pharmacist for a list of these medicines if you are not sure if you are taking any of the medicines listed above. Know the medicines you take. Keep a list of them to show your healthcare provider and pharmacist when you get a new medicine.

How should I take GoLYTELY?

You must read, understand, and follow these instructions to take GoLYTELY the right way.

- Take GoLYTELY exactly as your healthcare provider tells you to take it
- See the “Instructions for Use” on the bottle label for instructions on how to mix, take or give GoLYTELY.
- Do not take undissolved GoLYTELY powder that has not been mixed with water (diluted). It may increase your risk of nausea, vomiting and fluid loss (dehydration).
- Do not take other laxatives while taking GoLYTELY.
- Drink reconstituted solution at a rate of 8 ounces (240 ml) every 10 minutes. Rapid drinking of each portion is better than drinking small amounts.
- Do not eat or drink anything colored red or purple.
- Do not eat solid foods at least 2 hours before taking GoLYTELY. You may eat a light breakfast 2 hours before taking GoLYTELY. For best results, do not consume solid food for 3 to 4 hours before drinking GoLYTELY.
- Drink only water and clear liquids:
  • the day before your colonoscopy
  • while taking GoLYTELY
  • after taking GoLYTELY until 2 hours before your colonoscopy.
- Drink clear liquids before, during, and after you take GoLYTELY to avoid fluid loss (dehydrated). Examples of clear liquids are:
  • water • clear broth
  • clear fruit juices without pulp including apple, white grape, • clear soda
  or white cranberry
  • strained limeade or lemonade • gelatin (without added fruit or topping)
  • coffee or tea (Do not use any dairy or non-dairy creamer) • popsicles without pieces of fruit or fruit pulp
- You may experience some abdominal bloating and distention before the bowels start to move. If severe discomfort or distention occur, slow or temporarily stop (discontinue) drinking the solution and contact your healthcare provider.
- The first bowel movement should occur approximately one hour after you start drinking the solution.
- Continue drinking until the watery stool is clear and free of solid matter.

What are the possible side effects of GoLYTELY?

GoLYTELY can cause serious side effects, including:

- See Section “What is the most important information I should know about GoLYTELY?”
- changes in certain blood tests. Your healthcare provider may do blood tests before and after you take GoLYTELY to check your blood for changes. Tell your healthcare provider if you have any symptoms of too much fluid loss, including:
  • vomiting • stomach (abdominal) cramping
  • nausea � • headache
  • bloating • urinate less than usual
  • dizziness • trouble drinking clear liquid
- ulcers of the bowel or bowel problems (ischemic colitis). Tell your healthcare provider right away if you have severe stomach-area (abdomen) pain or rectal bleeding.

The most common side effects of GoLYTELY include:

• nausea • stomach (abdominal) cramps • anal irritation
• stomach (abdominal) fullness • vomiting • esophageal bleeding
• bloating • chest x-ray that shows water in
the lungs (infiltrate) after
vomiting or inhaling food or liquid
(aspirate).

Tell your healthcare provider if you have any side effect that bothers you or that does not go away.

These are not all the possible side effects of GoLYTELY. For more information, ask your healthcare provider or pharmacist. Call your doctor for medical advice about side effects. You may report side effects to FDA at 1-800-FDA-1088.

How should I store GoLYTELY?
• Store GoLYTELY in a sealed container at room temperature, between 59ºF to 86°F (15ºC to 30°C).
• Store mixed (reconstituted) solution of GoLYTELY at 36° to 46°F (2°C to 8°C). Do not freeze.
• Use mixed (reconstituted) solution of GoLYTELY within 48 hours.
• After 48 hours, throw away (discard) any mixed (reconstituted) solution of GoLYTELY that is not used.
Keep GoLYTELY and all medicines out of the reach of children.

General information about the safe and effective use of GoLYTELY.
Medicines are sometimes prescribed for purposes other than those listed in a Medication Guide. Do not use GoLYTELY for a condition for which it was not prescribed. Do not give GoLYTELY to other people, even if they are going to have the same procedure you are. It may harm them.
This Medication Guide summarizes important information about GoLYTELY. If you would like more information, talk with your healthcare provider. You can ask your pharmacist or healthcare provider for information that is written for healthcare professionals.

What are the ingredients in GoLYTELY?
GoLYTELY comes in a 4-liter jug with GoLYTELY powder.
Active ingredients:
Powder for solution: polyethylene glycol 3350, sodium sulfate (anhydrous), sodium bicarbonate, sodium chloride, and potassium chloride.

Manufactured by Braintree Laboratories, Inc.
270 Centre Street
Holbrook, MA 02343
Marketed by Braintree, a Part of Sebela Pharmaceuticals®
60 Columbian Street West
Braintree, MA 02185
For more information go to www.braintreelabs.com or call 1-800-874-6756.

This Medication Guide has been approved by the U.S. Food and Drug Administration.
Revised: 05/2021

PACKAGE LABEL

Principal Display Panel

FILL TO THE TOP OF THE LINE ON BOTTLE

NDC 52268-100-01

TO PHARMACIST AND PATIENT: Mixing information is on base label.

Package insert may be removed before dispensing.

Dispense the enclosed Medication Guide to each patient.

GoLYTELY®

PEG-3350 and Electrolytes for Oral Solution

When reconstituted with water to a volume of 4 liters, this solution contains PEG-3350 59 g/L, sodium sulfate 5.69 g/L, sodium bicarbonate 1.69 g/L, sodium chloride 1.47 g/L, and potassium chloride 0.743 g/L.

Each disposable jug contains, in powdered form: polyethylene glycol 236 g, sodium sulfate (anhydrous) 22.74 g, sodium bicarbonate 6.74 g, sodium chloride 5.86 g, potassium chloride 2.97 g.

RX only

Manufactured by Braintree Laboratories, Inc., Braintree, MA 02185

Marketed by Braintree, A part of Sebela Pharmaceuticals®

PACKAGE LABEL

FILL TO THE TOP OF THE LINE ON BOTTLE

NDC 52268-101-01

TO PHARMACIST AND PATIENT:
Mixing information is on base
label. Package insert may be
removed before dispensing. Dispense the enclosed Medication Guide to each patient.

Pineapple Flavor

GoLYTELY®

PEG-3350 and Electrolytes for Oral Solution

When reconstituted with water to a volume of 4 liters, this solution contains 125 mmol/L sodium , 10 mmol/L potassium, 40 mmol/L sulfate, 20 mmol/L bicarbonate, 35 mmol/L chloride and 17.6 mmol/L polyethylene glycol 3350.

Each disposable jug contains, in powdered form: polyethylene glycol 3350 236 g, sodium sulfate (anhydrous) 22.74 g, sodium bicarbonate 6.74 g, sodium chloride 5.86 g, potassium chloride 2.97 g, flavor ingredients 3.0 g.

RX only M 9/13

Braintree

Laboratories, Inc

Braintree, MA 02185

PACKAGE LABEL

NDC 52268-700-01
Rx only

GoLYTELY®
PEG-3350 AND ELECTROLYTES
FOR ORAL SOLUTION
1 Gallon (3.785 Liters)

Instructions

A GoLYTELY® solution is made up by dissolving the contents of this packet in one gallon of tap
water according to the following procedure:

Obtain a food-grade clear container with a volume of at least one gallon.
After cutting open the packet, pour the entire contents into the container.
Add lukewarm drinking water to bring the volume of the solution to one gallon.
Do not add any other ingredients, flavors, etc.
Shake and/or mix thoroughly to ensure that the ingredients are dissolved.
The solution is more palatable if chilled in the refrigerator before drinking. Keep reconstituted solution refrigerated. Use within 48 hours. Discard unused portion.
For best results, no solid food should be consumed for the 3 to 4 hour period before drinking the solution; but in no case should solid food be eaten within two hours of taking GoLYTELY.
Drink one 8 oz. glassful of the solution rapidly every 10 minutes. A loose watery bowel movement should result in approximately one hour. Continue drinking until the rectal effluent is clear or the entire contents (1 gallon) have been consumed or as directed by your physician.
Usual dosage: 1 gallon (3.785 liters).
This package contains:
Polyethylene glycol 3350…..227.1 grams
Sodium sulfate, anhydrous….21.5 grams
Sodium bicarbonate………….6.36 grams
Sodium chloride………………5.53 grams
Potassium chloride…………..2.82 grams

APPROXIMATE NET WEIGHT: 263 grams
Distributed by Braintree Laboratories, Inc., Braintree, MA 02185